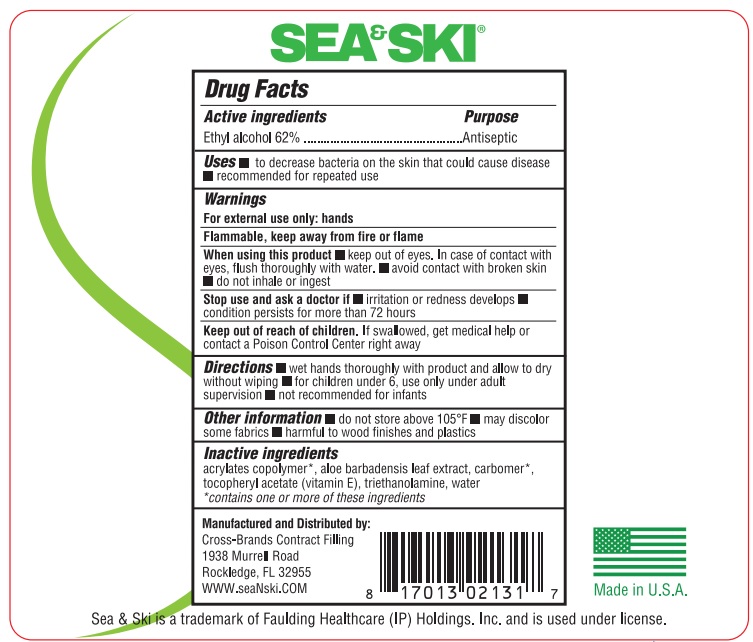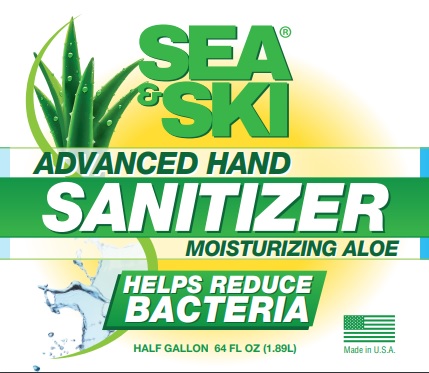 DRUG LABEL: Sea and Ski Advance Hand Sanitizer
NDC: 73440-3131 | Form: GEL
Manufacturer: Cross-Brands Contract Filling
Category: otc | Type: HUMAN OTC DRUG LABEL
Date: 20210219

ACTIVE INGREDIENTS: ALCOHOL 1171.73 g/1889.89 g
INACTIVE INGREDIENTS: WATER

Sea&Ski Advance Hand Sanitizer 64oz

Active Ingredient

Ethyl Alcohol 62%

Purpose

Antispetic

Uses

To decrease bacteria on the skin that could cause disease

Recommended for repeated use

Warnings

For external use only: Hands

Flammable, keep away from fire or flame

When using

When using this product keep out of eyes. In case of contact with eyes, flush thoroughly with water. Avoid contact with broken skin. D not inhale or ingest

Stop use

Stop Use and ask a doctor if irritation or redness develops condition persists for more than 72 hours.

Keep out of reach of children. If swallowed, get medical help or contact a Poison Control Center right away.

Directions

wet hands thoroughly with product and allow to dry without wiping for children under 6, use only under adult supervision not recommended for infants

Other information

do not store above 105°F may discolor some fabrics harmful to wood finishes and plastics

Inactive ingredients

acrylates copolymer*, aloe barbadensis leaf extract carbomer*, tocopheryl acetate (vitamin E), triethanolamine, water

*contains one or more of these ingredients